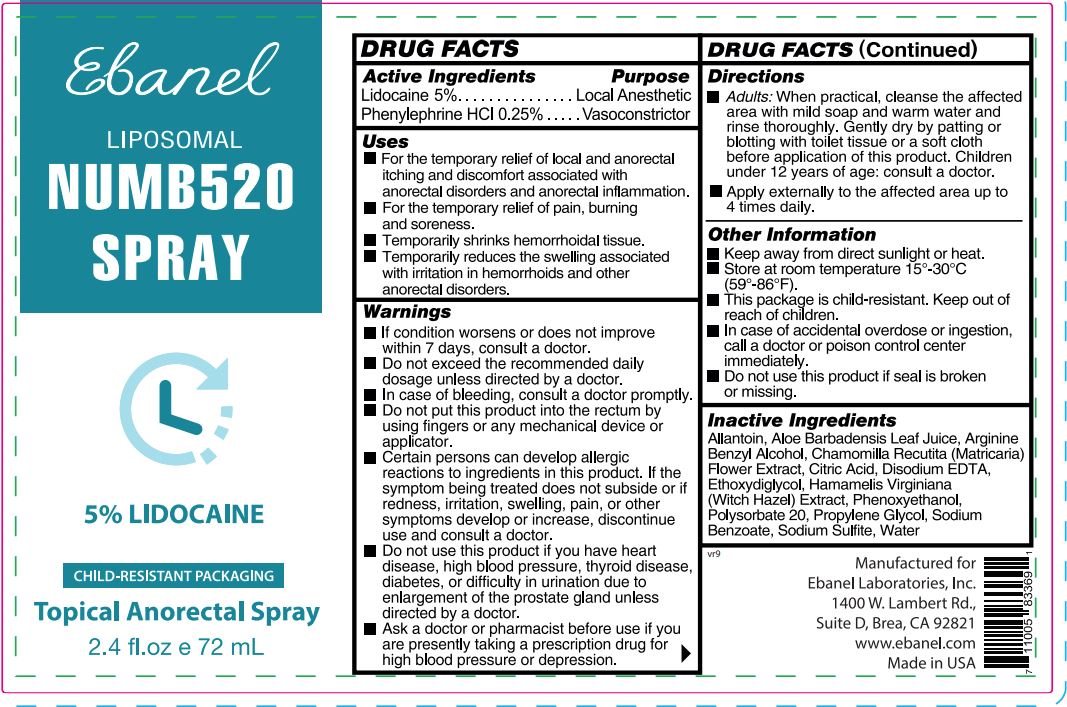 DRUG LABEL: Numb520
NDC: 63742-034 | Form: SPRAY
Manufacturer: Clinical Resolution Laboratory, Inc.
Category: otc | Type: HUMAN OTC DRUG LABEL
Date: 20250515

ACTIVE INGREDIENTS: LIDOCAINE 50 mg/1 mL; PHENYLEPHRINE HYDROCHLORIDE 2.5 mg/1 mL
INACTIVE INGREDIENTS: ALLANTOIN; ARGININE; BENZYL ALCOHOL; EDETATE DISODIUM ANHYDROUS; DIETHYLENE GLYCOL MONOETHYL ETHER; PHENOXYETHANOL; POLYSORBATE 20; WATER; SODIUM BENZOATE; SODIUM SULFITE

Numb520 SPRAY

Active Ingredient

Lidocaine 5%

Phenylephrine HCL 0.25%

Purpose

Local Anesthetic

Vasoconstrictor

Uses:

for the temporary relief of local and anorectal itching, discomfort, and pain associated with anorectal disorders or anorectal inflammation.

Warnings

- for external use only.
- avoid contact with the eyes.

Do not use

this product if

- pregnant or breastfeeding, ask a health professional before use.
- seal is broken or missing.
- you have heart disease, high blood pressure, thyroid disease, diabetes, or difficulty in urination due to enlargement of prostate gland unless directed by a doctor.

When using this product

- do not exceed the recommended daily usage.
- certain persons can develop allergic reactions to ingredients in this product.
- do not put this product into the rectum by using finger or any medical device or applicator.
- if swallowed, call your Poison Control Center at 1(800) 222 1222.
- If condition worsens or does not improve within 7 days, consult a doctor.

Stop use and ask a doctor if

- the symptom being treated does not subside, or redness, irritation, swelling, pain, or other symptoms develop or increase.

Directions

- clean the affected area.
- sensitivity and possible allergy tests advised prior to use. Spray sparingly to affected area after thoroughly cleansing. Wait until anesthetic effect occurs. You may reapply to continue numbing effect.
- apply to the affected area up to 4 times daily.
- children under 12 years of age: consult a doctor.

Other Information

- keep away from direct sunlight or heat.
- store at room temperature 15°-30°C (59°-86°F).

Inactive Ingredients

Allantoin, Arginine, Benzyl Alcohol, Disodium EDTA, Ethoxydiglycol, Phenoxyethanol, Polysorbate 20, Water, Sodium Benzoate, Sodium Sulfite